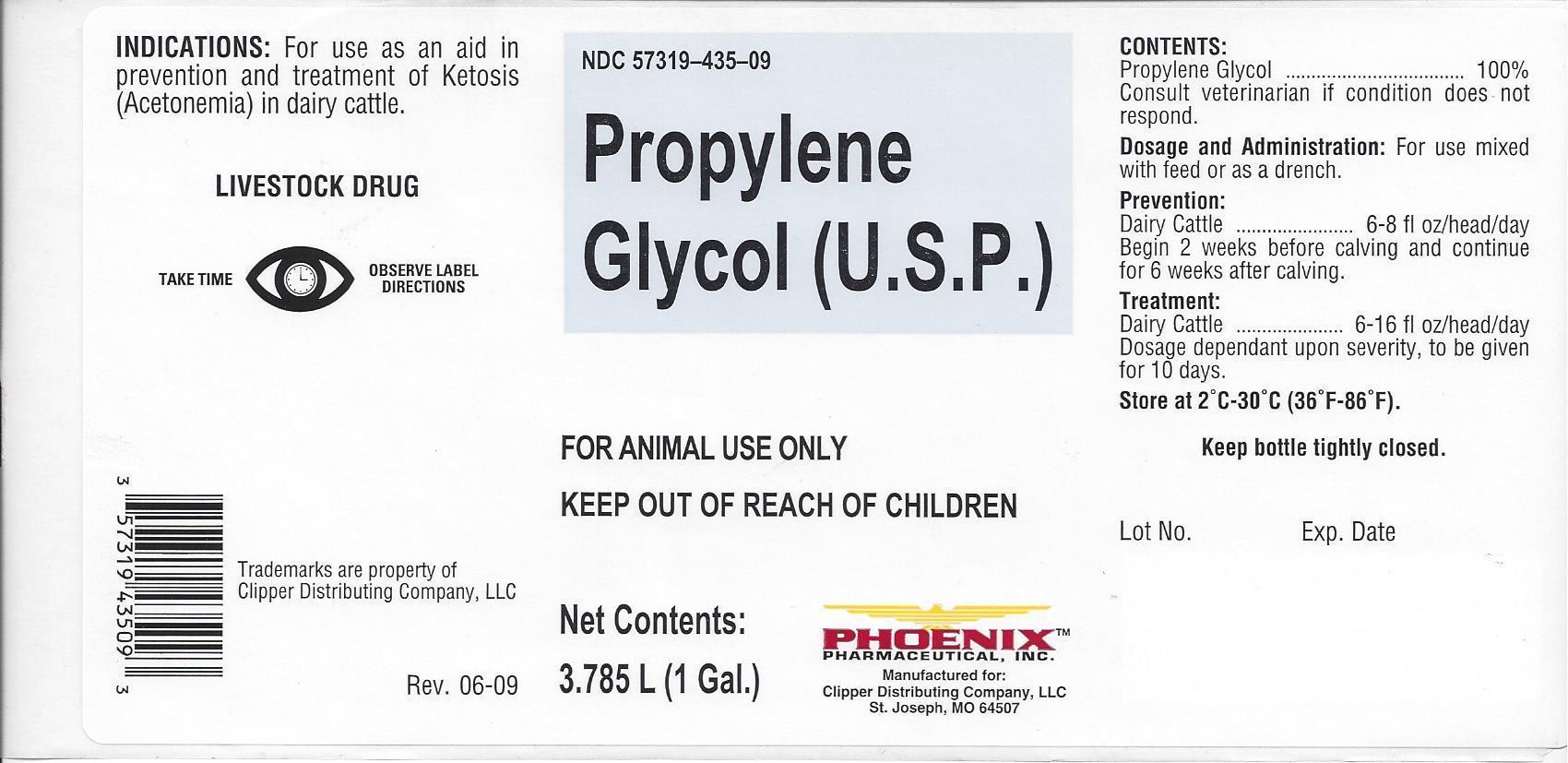 DRUG LABEL: PROPYLENE GLYCOL
NDC: 57319-435 | Form: LIQUID
Manufacturer: Phoenix Pharmaceutical Inc./Clipper Distributing, Inc.
Category: animal | Type: OTC ANIMAL DRUG LABEL
Date: 20130903

ACTIVE INGREDIENTS: PROPYLENE GLYCOL 3.45 kg/3.45 kg

PHOENIX PROPYLENE GLYCOL (U.S.P.)

NDC 57319-435-09 Propylene Glycol (U.S.P.)

FOR ANIMAL USE ONLY
KEEP OUT OF REACH OF CHILDREN

Net Contents:

3.785L (1 Gal.)

PHOENIX

Pharmaceutical, Inc.

Manufactured for:

Clipper Distributing Company, LLC

St. Joseph, MO 64507

INDICATIONS:

For use as an aid in prevention and treatment of Ketosis (Acetonemia) in dairy cattle.

LIVESTOCK DRUG

TAKE TIME OBSERVE LABEL DIRECTIONS

Tradmarks are property of Clipper Distributing Company, LLC

Rev. 06-09

CONTENTS:

Propylene Glycol............................100%

Consult veterinarian if condtion does not respond.

DOSAGE AND ADMINISTRATION:

For use mixed with feed or as a drench.

PREVENTION:

Dairy Cattle.....................6-8 fl oz/head/day

Begin 2 weeks before calving and continue for 6 weeks after calving.

TREATMENT:

Dairy Cattle....................6-16 fl oz/head/day

Dosage dependant upon severity, to be given for 10 days.

STORAGE AND HANDLING

Store at 2˚C - 30˚C (36˚F - 86˚F).

Keep bottle tightly closed.

Lot No. Exp Date